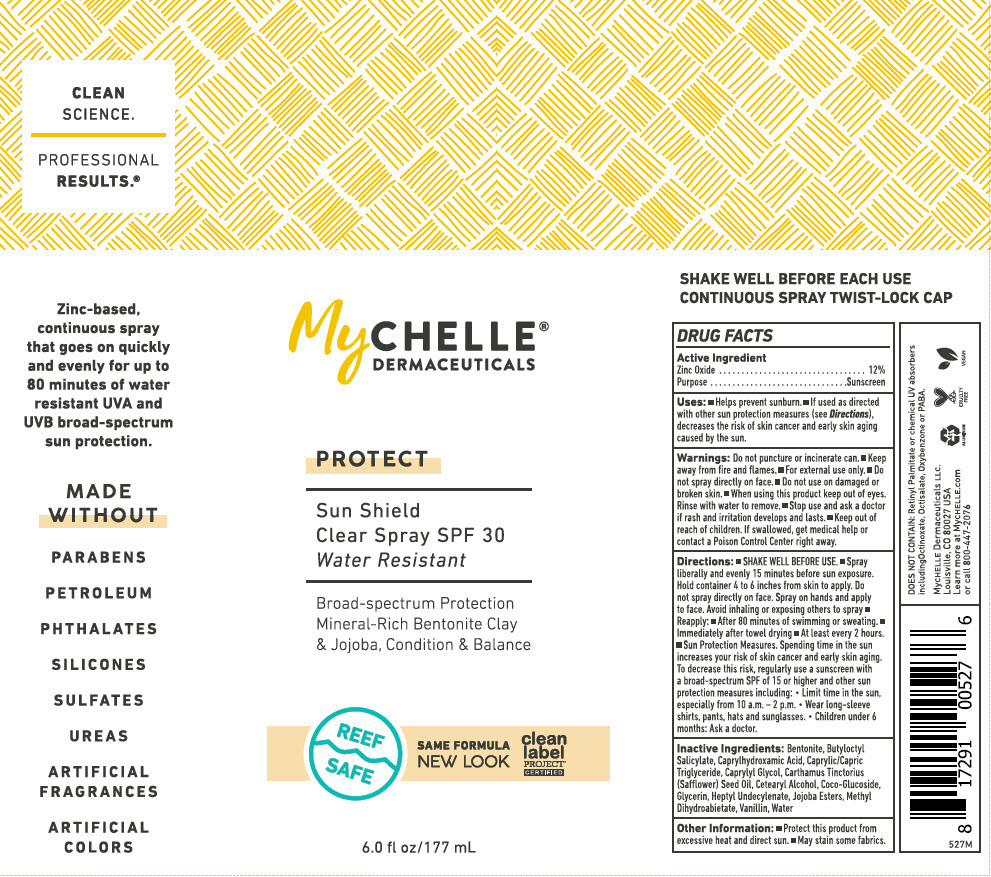 DRUG LABEL: MyChelle Dermaceuticals Sun Shield Clear SPF 30 
NDC: 72805-041 | Form: SPRAY
Manufacturer: French Transit, Ltd.
Category: otc | Type: HUMAN OTC DRUG LABEL
Date: 20220107

ACTIVE INGREDIENTS: Zinc Oxide 12 g/100 mL
INACTIVE INGREDIENTS: Water; Bentonite; Butyloctyl Salicylate; Caprylhydroxamic Acid; Medium-Chain Triglycerides; Caprylyl Glycol; Safflower Oil; Cetostearyl Alcohol; Coco Glucoside; Glycerin; Heptyl Undecylenate; HYDROGENATED JOJOBA OIL, RANDOMIZED; Methyl Dihydroabietate; Vanillin

MyChelle® Dermaceuticals Sun Shield Clear Spray SPF 30
Protect

DRUG FACTS

Active Ingredients

Zinc Oxide 12%

Purpose

Sunscreen

Uses

Helps prevent sunburn. If used as directed with other sun protection measures (see Directions), decreases the risk of skin cancer and early skin aging caused by the sun.

Warnings

Do not puncture or incinerate can.

- Keep away from fire and flames.
- For external use only.

- Do not use on damaged or broken skin.

- When using this product keep out of eyes.
- Rinse with water to remove.

- Stop use and ask a doctor if rash and irritation develops and lasts.

- Keep out of reach of children. If swallowed, get medical help or contact a Poison Control Center right away.

Directions

- SHAKE WELL BEFORE USE.
- Spray liberally and evenly 15 minutes before sun exposure. Hold container 4 to 6 inches from skin to apply. Do not spray directly on face. Spray on hands and apply to face. Avoid inhaling or exposing others to spray.
- Reapply:
  - After 80 minutes of swimming or sweating.
  - Immediately after towel drying
  - At least every 2 hours.
- Sun Protection Measures. Spending time in the sun increases your risk of skin cancer and early skin aging. To decrease this risk, regularly use a sunscreen with a broad spectrum SPF of 15 or higher and other sun protection measures including:
  Limit time in the sun, especially from 10 a.m. – 2 p.m.
  Wear long-sleeve shirts, pants, hats and sunglasses.
  Children under 6 months: ask a doctor.

Inactive Ingredients

Bentonite, Butyloctyl Salicylate, Caprylhydroxamic Acid, Caprylic/Capric Triglyceride, Caprylyl Glycol, Carthamus Tinctorius (Safflower) Seed Oil, Cetearyl Alcohol, Coco-Glucoside, Glycerin, Heptyl Undecylenate, Jojoba Esters, Methyl Dihydroabietate, Vanillin, Water

Other information

- Protect this product from excessive heat and direct sun.
- May stain some fabrics

PRINCIPAL DISPLAY PANEL - 177 mL Bottle Label

MyCHELLE®
DERMACEUTICALS

PROTECT

Sun Shield
Clear Spray SPF 30
Water Resistant

Broad-spectrum Protection
Mineral-Rich Bentonite Clay
& Jojoba, Condition & Balance

REEF
SAFE

SAME FORMULA
NEW LOOK

clean
label
PROJECT®
CERTIFIED

6.0 fl oz/177 mL